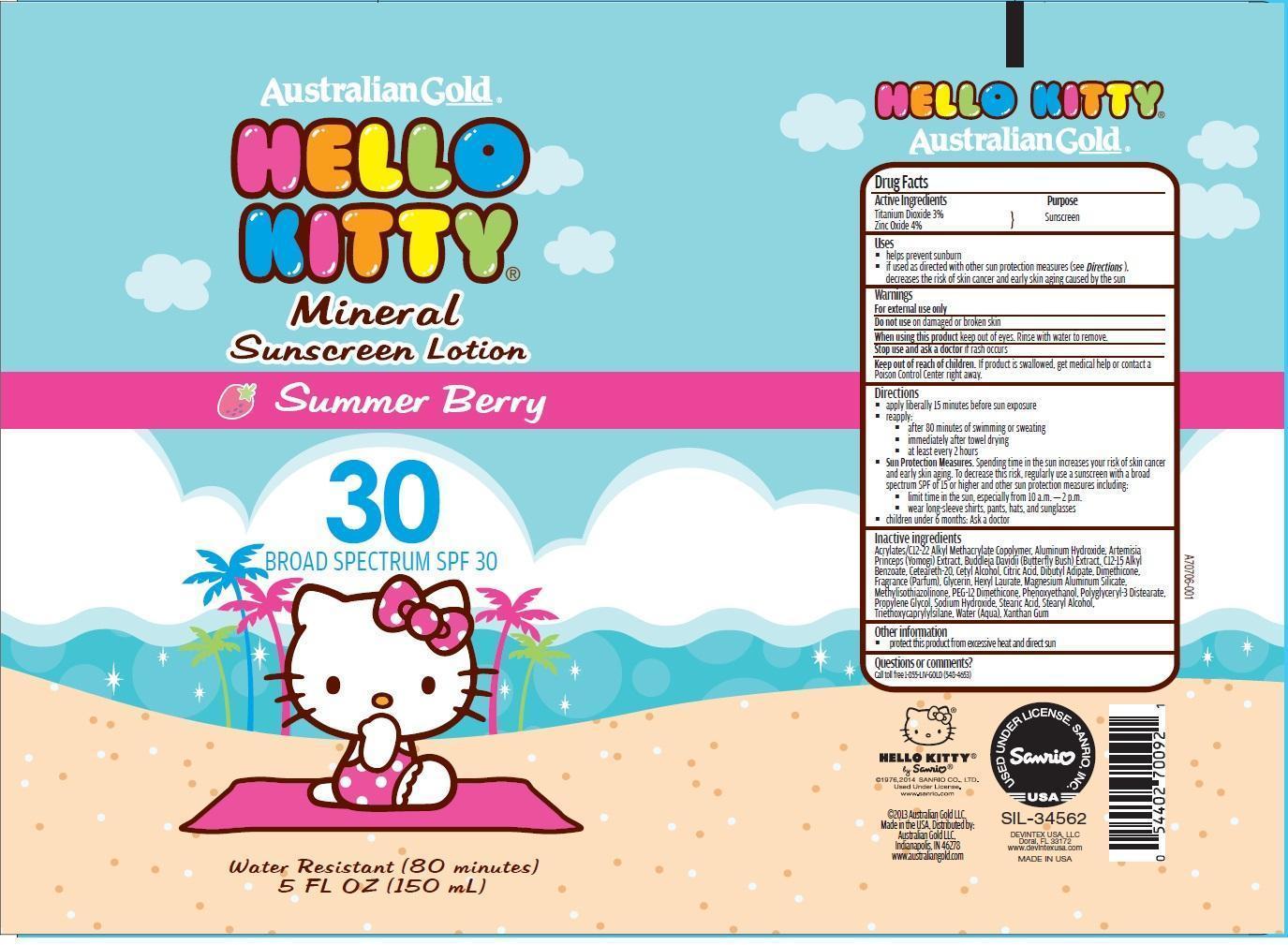 DRUG LABEL: Australian Gold
NDC: 58443-0081 | Form: LOTION
Manufacturer: Prime Enterprises, Inc.
Category: otc | Type: HUMAN OTC DRUG LABEL
Date: 20200117

ACTIVE INGREDIENTS: TITANIUM DIOXIDE 29.8 mg/1 mL; ZINC OXIDE 39.7 mg/1 mL
INACTIVE INGREDIENTS: ALUMINUM HYDROXIDE; STEARIC ACID; TRIETHOXYCAPRYLYLSILANE; BUTYL ACRYLATE/C16-C20 ALKYL METHACRYLATE/METHACRYLIC ACID/METHYL METHACRYLATE COPOLYMER; ALKYL (C12-15) BENZOATE; POLYOXYL 20 CETOSTEARYL ETHER; CETYL ALCOHOL; CITRIC ACID MONOHYDRATE; DIBUTYL ADIPATE; DIMETHICONE; GLYCERIN; HEXYL LAURATE; MAGNESIUM ALUMINUM SILICATE; METHYLISOTHIAZOLINONE; PEG-12 DIMETHICONE/PPG-20 CROSSPOLYMER; PHENOXYETHANOL; POLYGLYCERYL-3 DISTEARATE; SODIUM HYDROXIDE; STEARYL ALCOHOL; WATER; PROPYLENE GLYCOL; BUDDLEJA DAVIDII LEAF; ARTEMISIA PRINCEPS LEAF; XANTHAN GUM

Active ingredients

Titanium Dioxide 3 % and Zinc Oxide 4 %

Purpose

Sunscreen

Uses

- helps prevent sunburn
- if used as directed with other sun protection measure (see Directions), decreases the risk of skin cancer and early skin aging caused by the sun

Warnings

OTHER SAFETY INFORMATION

For external use only

Do not use on damaged or broken skin.

When using this product keep out of eyes. Rinse with water to remove.

Stop use and ask a doctor if rash occurs.

Keep out of reach of children. If product is swallowed, get medical help or contact a Poison Control Center right away.

Directions

- apply liberally 15 minutes before sun exposure
- reapply:
  - after 80 minutes of swimming or sweating
  - immediately after towel drying
  - at least every 2 hours
- Sun Protection Measures. Spending time in the sun increases your risk of skin cancer and early skin aging. To decrease this risk, regularly use a sunscreen with a broad spectrum SPF of 15 or higher and other sun protection measures including:
  - limit time in the sun especially from 10 a.m. – 2 p.m.
  - wear long-sleeve shirts, pants, hats, and sunglasses
- children under 6 months: Ask a doctor

Inactive Ingredients

Acrylates/C12-22 Alkyl Methacrylate Copolymer, Aluminum Hydroxide, Artemisia Princeps (Yomogi) Extract, Buddleja Davidii (Butterfly Bush) Extract, C12-15 Alkyl Benzoate, Ceteareth-20, Cetyl Alcohol, Citric Acid, Dibutyl Adipate, Dimethicone, Fragrance (Parfum), Glycerin, Hexyl Laurate, Magnesium Aluminum Silicate, Methylisothiazolinone, PEG-12 Dimethicone, Phenoxyethanol, Polyglyceryl-3 Distearate, Propylene Glycol, Sodium Hydroxide, Stearic Acid, Stearyl Alcohol, Triethoxycaprylylsilane, Water (Aqua), Xanthan Gum

Other information

- protect this product from excesive heat and direct sun

Questions or Comments?

Call toll free 1-855-LIV-GOLD (548-4653)

PRINCIPAL DISPLAY PANEL - 150 mL Bottle Label

Australian Gold

HELLO

KITTY

Mineral

Sunscreen Lotion

Summer Berry

30

BROAD SPECTRUM SPF 30

Water Resistant (80 minutes)

5 FL OZ (150 mL)